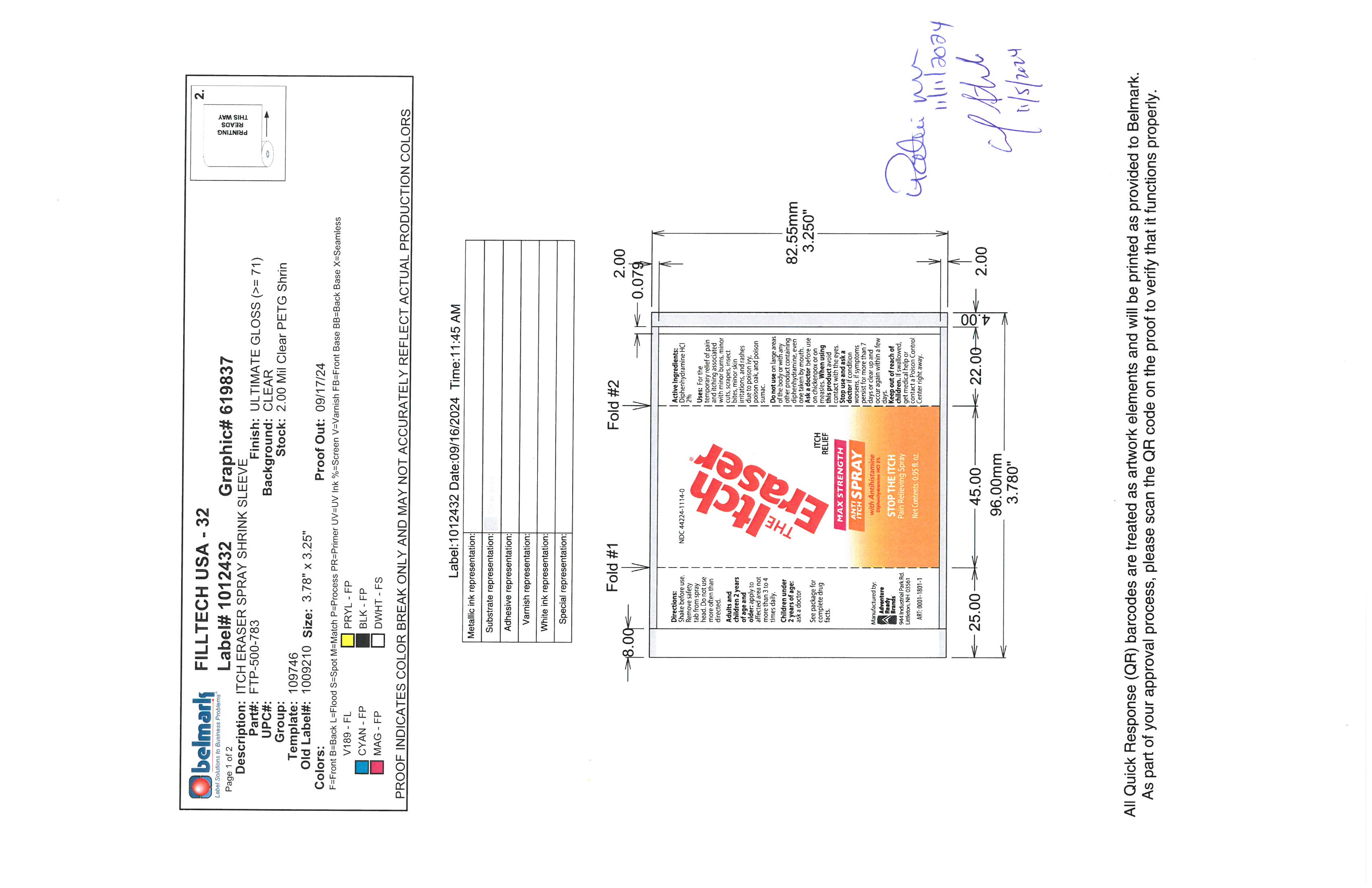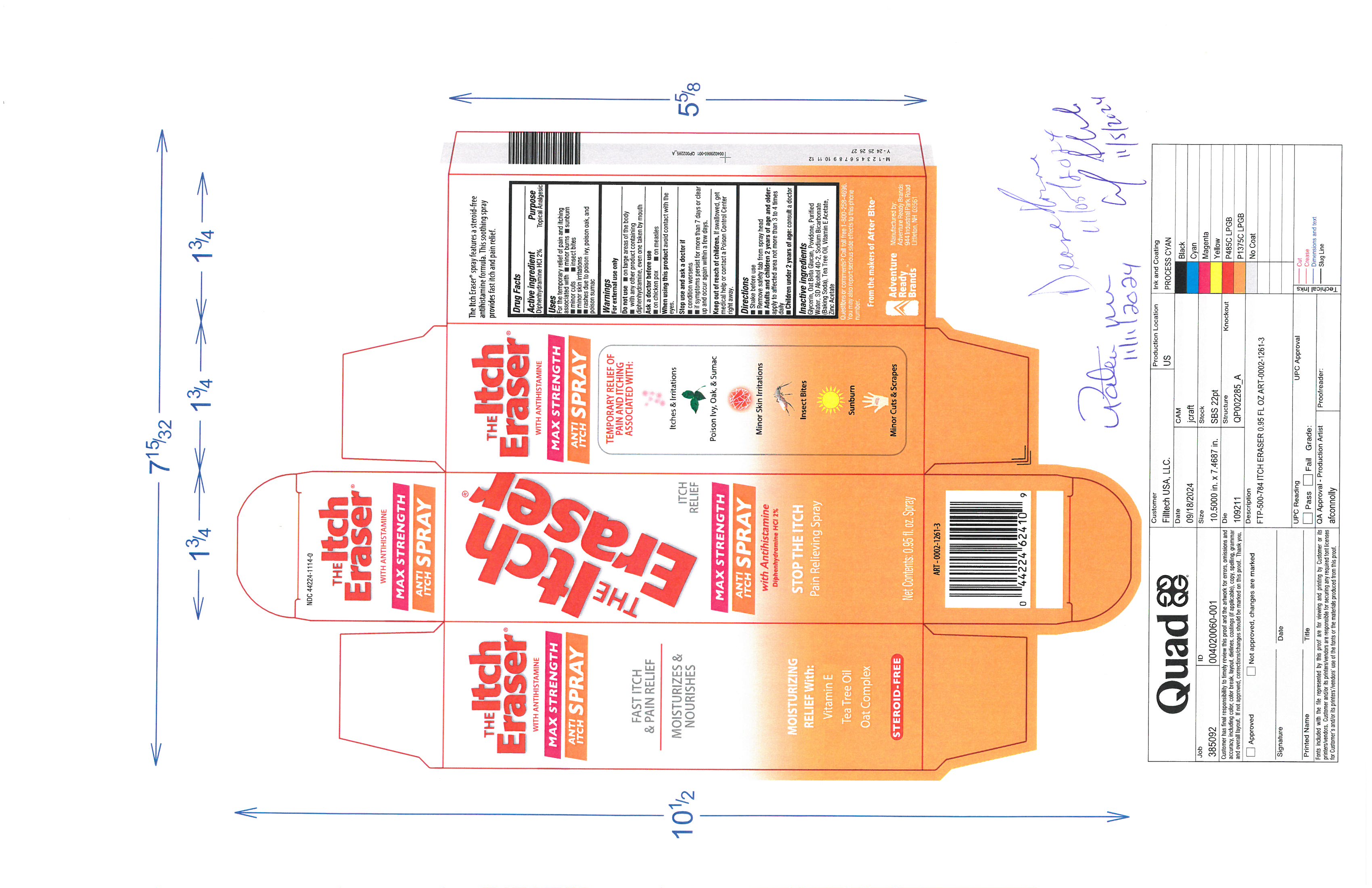 DRUG LABEL: Itch Eraser
NDC: 44224-1114 | Form: SPRAY
Manufacturer: Tender Corporation d/b/a Adventure Ready Brands
Category: otc | Type: HUMAN OTC DRUG LABEL
Date: 20251118

ACTIVE INGREDIENTS: DIPHENHYDRAMINE HYDROCHLORIDE 0.51 g/25.5 g
INACTIVE INGREDIENTS: TEA TREE OIL 0.128 g/25.5 g; POVIDONE K30 0.77 g/25.5 g; WATER 4.05 g/25.5 g; OAT 0.51 g/25.5 g; ZINC ACETATE 0.026 g/25.5 g; SODIUM BICARBONATE 0.128 g/25.5 g; .ALPHA.-TOCOPHEROL ACETATE 0.128 g/25.5 g; GLYCERIN 0.77 g/25.5 g; ALCOHOL 18.48 g/25.5 g

Itch Eraser Spray

Active Ingredient

Diphenhydramine HCl 2%

Purpose

Topical Analgesic

Uses

For the temporary relief of pain and itching associated with, minor burns, sunburn,minor cuts, insects bites, minor skin irritations, rashes due to poison ivy, poison oak, and poison sumac

Warnings

For external use only

Do not use

on large areas of the body, with any other product containing diphenhydramine, even one taken by mouth

Ask a doctor before use

on chicken ox, measles

when using this product

avoid contact with eyes.

Stop use and ask a doctor if

condition worses, if symptoms persist for more than 7 days or clear up and occur again within a few days.

Keep out of reach of children

if swallowed, get medical help or contact poison control center right away.

Directions

Shake before use

remove safety tab from spray head

adults and children 2 years of age and older: apply to affected area not more than 3 to 4 times daily.

children under 2 years of age: consult a doctor

Inactive Ingredients

glycerinm oat beta glucanm povidone, purified water, sd alcohol 40-2, sodium bicarbonate (baking soda), tea tree oil, vitamine e acetate, zinc acetate